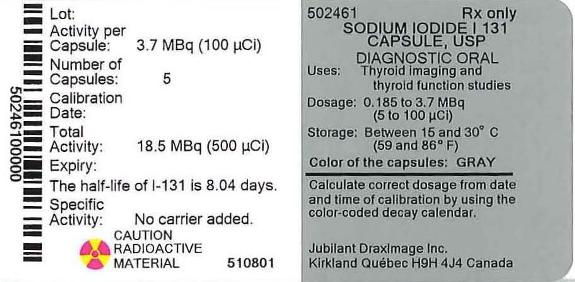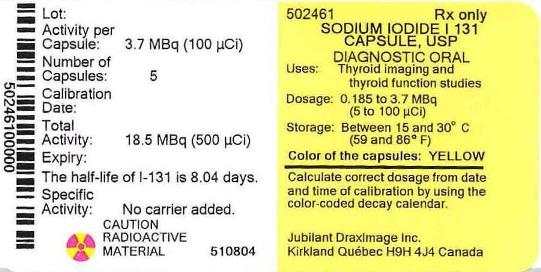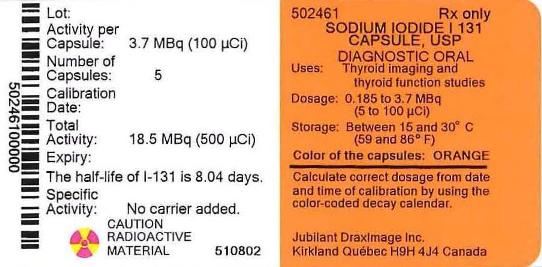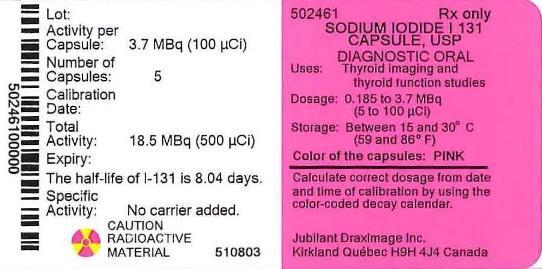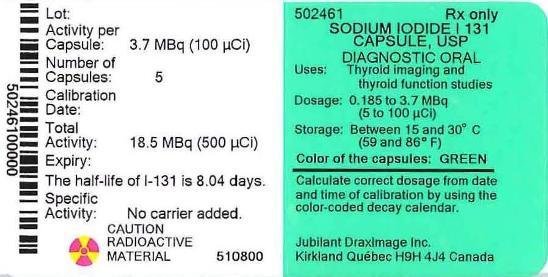 DRUG LABEL: Sodium Iodide I 131  Diagnostic 
NDC: 65174-461 | Form: CAPSULE
Manufacturer: Jubilant DraxImage Inc., dba Jubilant Radiopharma
Category: prescription | Type: HUMAN PRESCRIPTION DRUG LABEL
Date: 20200825

ACTIVE INGREDIENTS: Sodium Iodide I-131 100 mCi/1 1
INACTIVE INGREDIENTS: Edetate Disodium; Sodium Thiosulfate; Sodium Phosphate, Dibasic, Anhydrous

HIGHLIGHTS OF PRESCRIBING INFORMATION

These highlights do not include all the information needed to use SODIUM IODIDE I 131 CAPSULES DIAGNOSTIC safely and effectively. See full prescribing information for SODIUM IODIDE I 131 CAPSULES DIAGNOSTIC.
SODIUM IODIDE I 131 capsules, diagnostic, for oral use.
Initial U.S. Approval: 1971

RECENT MAJOR CHANGES

Indications and Use. (1) 6/2016

1 INDICATIONS AND USAGE

Sodium Iodide I 131 Capsules Diagnostic is a radioactive diagnostic agent indicated for the assessment of thyroid function and for thyroid imaging.

2 DOSAGE AND ADMINISTRATION

- Use careful handling with appropriate safety measures to minimize radiation exposure to patients and healthcare workers. (2.1, 5.2)
- Follow suitable radioactivity calibration prior to administration. (2.1)
- In an adult patient, recommended doses are (2.2):
  - Thyroid Function: 0.185 to 1.1 megabecquerels (MBq) [5 to 30 microcuries (microCi)]
  - Thyroid Imaging: 1.85 to 3.70 MBq (50 to 100 microCi)

3 DOSAGE FORMS AND STRENGTHS

Capsules: 3.70 MBq (100 microCi) at the time of calibration

4 CONTRAINDICATIONS

Pregnancy

5 WARNINGS AND PRECAUTIONS

- Fetal Toxicity – I 131 can cause severe and irreversible hypothyroidism in the neonate. Verify absence of pregnancy before administering the product. (4, 5.1, 8.1, 8.3)
- Radiation Risk – I 131 contributes to patients’s long-term cumulative radiation exposure, which is associated with an increased risk of cancer. Ensure safe handling to minimize radiation exposure. (5.2)

6 ADVERSE REACTIONS

Common adverse reactions reported with diagnostic doses of sodium iodide I 131 include nausea, vomiting, itching, rash and hives. (6)

To report SUSPECTED ADVERSE REACTIONS, contact Jubilant DraxImage Inc. at 1-888-633-5343 or FDA at 1-800-FDA-1088 or www.fda.gov/medwatch.

7 DRUG INTERACTIONS

The recent intake of iodine in any form or the use of thyroid or anti-thyroid drugs will affect the uptake of sodium iodide I 131. (5.3, 7)

8 USE IN SPECIFIC POPULATIONS

- Lactation: Discontinue breastfeeding. (8.2)
- Renal Impairment: Increases radiation exposure. (8.6)

FULL PRESCRIBING INFORMATION

1 INDICATIONS AND USAGE

Sodium Iodide I 131 Capsules Diagnostic is indicated for use in adults for:

- Assessment of thyroid function using radioactive iodine (RAI) uptake test
- Imaging the thyroid (scintigraphy)

2 DOSAGE AND ADMINISTRATION

2.1 Radiation Safety

Sodium Iodide I 131 Capsules Diagnostic is a radioactive drug and should be handled with appropriate safety measures to minimize radiation exposure to the patient and healthcare worker [see Warnings and Precautions (5.2)].

- Use waterproof gloves during the entire handling and administration procedure.
- Maintain adequate shielding during the life of the product.
- Open the capsule-containing vial in a well ventilated hood to avoid exposure to trace levels of volatile I-131 which may be present.
- Measure patient dose by a suitable radioactivity calibration system immediately prior to administration.

2.2 Recommended Dosage and Administration Instructions

Administer Sodium Iodide I 131 Capsules Diagnostic orally prior to scanning. The recommended dose of Sodium Iodide I 131 Capsules Diagnostic for an adult patient is the following:

- Thyroid Function: 0.185 to 1.1 megabecquerels (MBq) [5 to 30 microcuries (microCi)]. Administer 24 hours before uptake measurement.
- Thyroid Imaging (Scintigraphy): 1.85 to 3.70 MBq (50 to 100 microCi). Administer 16 -24 hours before imaging.

Consult the color-coded decay calendar that is updated in January of every year to determine which colored capsule(s) correspond to the prescribed dose: https://www.draximage.com/products/us/draximage-i-131-diagnostic-capsules/ or calculate the correct dose from the date and time of calibration provided on the container label.

Prior to Sodium Iodide I 131 Capsules Diagnostic Administration

- Obtain a pregnacy test in females of reproductive potential prior to administration to verify the absence of pregnancy [see Contraindications (4) and Use in Specific Populations (8.1, 8.3)].
- Advise patients to maintain a low-iodine diet two weeks prior to radioiodine administration and continue for several days during the uptake or imaging process [see Drug Interactions (7)].
- Advise patients to fast at least 2 hours before and 2 hours after administration to ensure absorption.
- Advise patients to hydrate before and after administration of radioiodine and void frequently to ensure rapid excretion.

2.3 Radiation Dosimetry

The biokinetic and radiation dose distributions associated with thyroid uptake of iodide I 131 depend on dietary intake of stable iodine. A range of uptake percentages in an average adult (73.7 kg) are shown in Table 1. For a thyroid blocked from iodide uptake in the production of hormones, the effective half-life of iodide I 131 is approximately 1.4 hours; for "low" to "high" uptake, the effective half-life of I 131 ranges from approximately 80 to 90 hours.

Table 1 Absorbed dose per unit activity sodium iodide I 131 administered orally (mGy/MBq) in adult (73.7-kg reference model)
Organ | Thyroid uptake of I 131 (% administered activity A0) 24 h after oral administration
Organ | Blocked thyroid (0% A0) | Low uptake (16% A0) | Medium uptake (26% A0) | High uptake (36% A0)
Adrenals | 0.044 | 0.051 | 0.055 | 0.059
Bone surfaces | 0.030 | 0.089 | 0.12 | 0.16
Brain | 0.021 | 0.093 | 0.13 | 0.17
Breast | 0.020 | 0.038 | 0.048 | 0.058
Gallbladder wall | 0.037 | 0.043 | 0.046 | 0.049
Gastrointestinal tract
Stomach wall | 0.87 | 0.77 | 0.71 | 0.66
Small intestine wall | 0.035 | 0.033 | 0.032 | 0.032
Colon wall | 0.14 | 0.14 | 0.14 | 0.14
(Upper large intestine wall) | 0.12 | 0.12 | 0.12 | 0.12
(Lower large intestine wall) | 0.17 | 0.17 | 0.17 | 0.16
Heart wall | 0.062 | 0.089 | 0.10 | 0.12
Kidneys | 0.27 | 0.27 | 0.27 | 0.27
Liver | 0.050 | 0.093 | 0.12 | 0.14
Lungs | 0.053 | 0.10 | 0.13 | 0.15
Muscles | 0.026 | 0.084 | 0.12 | 0.15
Oesophagus | 0.024 | 0.10 | 0.14 | 0.19
Ovaries | 0.038 | 0.037 | 0.036 | 0.035
Pancreas | 0.060 | 0.064 | 0.066 | 0.068
Red marrow | 0.031 | 0.072 | 0.095 | 0.12
Salivary glands | 0.27 | 0.22 | 0.19 | 0.16
Skin | 0.019 | 0.043 | 0.057 | 0.071
Spleen | 0.064 | 0.069 | 0.072 | 0.075
Testes | 0.025 | 0.024 | 0.023 | 0.22
Thymus | 0.024 | 0.10 | 0.14 | 0.19
Thyroid | 2.2 | 280 | 430 | 580
Urinary bladder wall | 0.54 | 0.45 | 0.39 | 0.34
Uterus | 0.045 | 0.042 | 0.040 | 0.038
Remaining organs | 0.029 | 0.84 | 0.11 | 0.15
Effective dose per administered activity (mSv/MBq) | 0.28 | 14 | 22 | 29

3 DOSAGE FORMS AND STRENGTHS

Capsules: Each capsule contains 3.70 MBq (100 microCi) at time of calibration. Half of each capsule is white, while the other half is either pink, yellow, orange, grey or green according to the manufactured lot. The capsule will yield 2.03, 1.11, 0.61, or 0.33 MBq (55, 30, 16.5, or 9 microCi) according to the color-coded decay calendar which assigns a color and capsule activity for each week of the year. https://www.draximage.com/products/us/draximage-i-131-diagnostic-capsules/

Table 2 below displays the (5) weeks activity of the capsule starting from the calibration day.

Table 2 Weekly Activity (MBq and microCi) of Each Capsule Starting from the Calibration Day
Week | Activity (MBq) | Activity (microCi)
1 | 3.70 | 100.0
2 | 2.03 | 54.9
3 | 1.11 | 30.0
4 | 0.61 | 16.5
5 | 0.33 | 8.9

4 CONTRAINDICATIONS

Sodium Iodide I 131 Capsules Diagnostic is contraindicated in pregnancy [see Warnings and Precautions (5.1), Use in Specific Populations (8.1)].

5 WARNINGS AND PRECAUTIONS

5.1 Fetal Toxicity

Sodium Iodide I 131 Capsules Diagnostic is contraindicated in pregnancy because sodium iodide I 131 crosses the placenta and can cause severe and irreversible hypothyroidism in the neonate. Multiple reports in the literature describe neonatal hypothryroidism following in utero exposure to sodium iodide I 131. Some of these cases were severe and irreversible. Verify pregnancy status of females of reproductive potential prior to administering Sodium Iodide I 131 Capsules Diagnostic [see Use in Specific Populations (8.1, 8.3)].

5.2 Radiation Exposure

Sodium Iodide I 131 Capsules Diagnostic contributes to a patient’s overall long-term cumulative radiation exposure, which is associated with an increased risk of cancer. Follow safe administration instructions to minimize radiation exposure to the patient and healthcare providers [see Dosage and Administration (2.1)].

5.3 Risk of Radioactive Uptake Measurement and Imaging Misinterpretation

The recent intake of stable iodine in any form, or the use of thyroid or anti-thyroid drugs will affect the uptake of sodium iodide I 131. Question the patient carefully regarding their exposure to these drugs or procedures involving radiographic contrast media [see Drug Interactions (7)].

5.4 Hypersensitivity Reactions

Hypersensitivity reactions including anaphylaxis may occur in patients who receive sodium iodide I 131. Although iodine is not considered an allergen, hypersensitivity reactions may occur in relation with excipients or chemical component of the capsule, such as sodium thiosulfate. Obtain and document an allergy history, particularly a sulfite allergy. Emergency resuscitation equipment and personnel should be immediately available [see Adverse Reactions (6)].

6 ADVERSE REACTIONS

The following adverse reaction has been described elsewhere in the labeling:

- Hypersensitivity Reactions [see Warnings and Precautions (5.4)]

The following adverse reactions have been identified during post-approval use from Sodium Iodide I 131 Capsules Diagnostic. Because these reactions are voluntarily reported from a population of uncertain size, it is not always possible to reliably estimate their frequency or establish a causal relationship to drug exposure.

Adverse reactions associated with the administration of Sodium Iodide I 131 Capsules Diagnostic are:

- Gastrointestinal disorders: vomiting, nausea, and diarrhea
- General disorders and administration site conditions: local thyroid swelling
- Immune system disorders: hypersensitivity reactions
- Skin and subcutaneous tissue disorders: itching, rash, hives, and erythema

7 DRUG INTERACTIONS

Certain drugs and iodine-containing foods interfere with the accumulation of radioiodide by the thyroid. Review the patients history, current medications, and recent diagnostic tests prior to the administration of Sodium Iodide I-131 Capsules Diagnostic. Advise patients to maintain a low-iodine diet two weeks prior to radioiodine administration and continue for several days during the uptake or imaging process and to discontinue the following products before they undergo the procedure as shown in Table 3:

Table 3 Pharmaceuticals/OTCs/Agents Blocking Radioiodine Uptake
Products | Recommended duration of withdrawal
Thionamide medications (e.g., propylthiouracil, methimazole carbimazole) | 3 days
Multivitamins containing iodide | 10 days
Natural or synthetic thyroid hormones triiodothyronine thyroxine | 2 weeks; 4 weeks
Iodine containing foods: iodinized salt, dairy products, egg yolks, seafood, turkey, and liver | 2 weeks
Kelp, agar, carrageenan, Lugol solution | 3 weeks
Saturated solution of potassium iodide | 3 weeks
Topical iodine (e.g., surgical skin preparation) | 3 weeks
Radiographic contrast agents Water soluble Lipophilic | 2 months; 6 months
Amiodarone | 6 months

8 USE IN SPECIFIC POPULATIONS

8.1 Pregnancy

Risk Summary

Sodium Iodide I 131 Capsules Diagnostic is contraindicated in pregnancy because fetal exposure can lead to neonatal hypothyroidism, which in some cases is severe and irreversible. Data from the published literature describe reports of neonatal thyroid abnormalities after fetal exposure, including agenesis of the thyroid and hypothyroidism (see Clinical Considerations, Data). No animal reproductive studies have been conducted.

The estimated background risk of major birth defects and miscarriage for the indicated population is unknown. In the U.S. general population, the estimated background risk of major birth defects and miscarriage in clinically recognized pregnancies are 2-4% and 15-20%, respectively.

Clinical Considerations

Fetal/Neonatal Adverse Reactions

A fetus exposed to sodium iodide I 131 can develop neonatal hypothyroidism. Delay in diagnosis of neonatal hypothyroidism after exposure to sodium iodide I 131 in utero can result in severe sequelae such as decreased mental capacity and delayed skeletal maturation. Monitor thyroid function in any infant born after in utero exposure to sodium iodide I 131.

Data

Human Data

Literature reports of maternal exposures to sodium iodide I 131 at doses of 330-8300 MBq during 4-26 weeks estimated gestational age. There were various adverse pregnancy outcomes; the most common was hypothyroidism in infants and children.

8.2 Lactation

Risk Summary
Advise women to discontinue breastfeeding after administration of Sodium Iodide I 131 Capsules Diagnostic. Infant exposure to sodium iodide I 131 via breast milk is expected and may lead to hypothyroidism in the infant because sodium iodide I 131 in breast milk may reach concentrations equal to or greater than concentrations in maternal plasma (see Data).

Data
Published studies show that sodium iodide I 131 is transferred into breast milk and is taken up by the thyroid of the breastfed infant.

8.3 Females and Males of Reproductive Potential

Sodium Iodide I 131 is contraindicated in pregnancy because it causes fetal hypothyroidism [see Use in Specific Populations (8.1) and Warnings and Precautions (5.1)].

Pregnancy Testing
Obtain a pregnancy test in females of reproductive potential and verify the absence of pregnancy before administering Sodium Iodide I 131 Capsules Diagnostic [see Dosage and Administration (2.2)].

8.4 Pediatric use

Safety and efficacy in pediatric patients have not been established. Published reports suggest that the thyroid gland of pediatric patients is more sensitive to the adverse effects of sodium iodide I 131 (e.g., increased risk of radiation absorption).

8.5 Geriatric Use

Clinical experience has not identified differences in safety or effectiveness in geriatric patients compared to younger patients. However, elderly patients are more likely to have decreased renal function and radiation exposure is greater in patients with impaired renal function [see Use in Specific Populations (8.6), Clinical Pharmacology (12.3)].

8.6 Renal Impairment

Radiation exposure following Sodium Iodide I 131 Capsules Diagnostic is greater in patients with impaired renal function compared to patients with normal renal function [see Clinical Pharmacology (12.3)].

10 OVERDOSAGE

In the event of an overdosage of Sodium Iodide I 131 Capsules Diagnostic, monitor for thyroid suppression and consider administering a thyroid blocking agent (e.g. potassium iodide (KI) or perchlorate). Promote frequent voiding and encourage patients to maintain hydration to minimize radiation exposure.

11 DESCRIPTION

11.1 Chemical Characteristics

Sodium Iodide I 131 Capsules Diagnostic is a radiodioactive diagnostic agent containing sodium iodide I 131 and supplied for oral administration in a gelatin capsule. Each capsule contains no-carrier-added sodium iodide I 131, disodium edetate dihydrate USP as a stabilizer, sodium thiosulfate pentahydrate USP as a reducing agent, and dibasic sodium phosphate anhydrous USP.

Sodium Iodide I 131 is designated chemically as Na131I and has a molecular weight of 153.99.

11.2 Physical Characteristics

Iodine I 131 decays by beta emission and associated gamma emission with a physical half-life of 8.04 days. The principal radiation emissions are listed in Table 4.

Table 4 Principal Radiation Emission Data from Decay of Sodium Iodide I 131
Radiation | Mean % per Disintegration | Mean Energy (keV)
Beta-1 | 2.13% | 69.4
Beta-3 | 7.20% | 96.6
Beta-4 | 89.4% | 191.6
Gamma-7 | 6.14% | 284.3
Gamma-14 | 81.2% | 364.5
Gamma-18 | 7.12% | 637.0

11.3 External Radiation

The specific gamma-ray constant for iodine I 131 is 4.26 x 10^-13 C•m^2•kg^-1•MBq^-1•s^-1 (2.2 R•cm^2/mCi•hr). The first half-value thickness of lead (Pb) for iodine I 131 is 0.27 cm. A range of values for the relative attenuation of the radiation emitted by iodine I 131 that results from interposition of various thicknesses of Pb is shown in Table 5. For example, the use of 2.59 cm of Pb will decrease the external radiation exposure by a factor of about 100.

Table 5 Radiation Attenuation of Iodine I 131 by Lead Shielding
Shield Thickness (Pb) cm | Coefficient of Attenuation
0.27 | 0.5
0.56 | 0.25
0.99 | 10^-1
2.59 | 10^-2
4.53 | 10^-3

To correct for physical decay of iodine I 131, the fractions that remain at selected intervals after the time of calibration are shown in Table 6.

Table 6 Physical Decay Chart: Iodine I 131, Half-Life 8.04 days
Days | Fraction Remaining | Days | Fraction Remaining | Days | Fraction Remaining
0 [Calibration Time] | 1.000 | 11 | 0.388 | 22 | 0.151
1 | 0.918 | 12 | 0.356 | 23 | 0.138
2 | 0.842 | 13 | 0.327 | 24 | 0.127
3 | 0.773 | 14 | 0.300 | 25 | 0.116
4 | 0.709 | 15 | 0.275 | 26 | 0.107
5 | 0.651 | 16 | 0.253 | 27 | 0.098
6 | 0.597 | 17 | 0.232 | 28 | 0.090
7 | 0.548 | 18 | 0.213 | 29 | 0.083
8 | 0.503 | 19 | 0.195 | 30 | 0.076
9 | 0.461 | 20 | 0.179
10 | 0.423 | 21 | 0.164

12 CLINICAL PHARMACOLOGY

12.1 Mechanism of Action

Iodine is actively transported by the sodium-iodide symporter (NIS) protein, in thyroid follicular cells. Iodide is concentrated in follicular cells up to 50 times higher than in the plasma. Iodide is metabolically oxidized by thyroid peroxidase to iodinium (I^+) which in turn iodinates tyrosine residues of thyroglobulin (tri or tetra-iodinated tyrosine). The gamma emission of Iodine I 131 is imaged or counted.

12.3 Pharmacokinetics

Absorption
Following oral administration of Sodium Iodide I 131 Capsules Diagnostic, 90% of the administered radioactivity of sodium iodide I 131 is systemically absorbed in the first 60 minutes.

Distribution
Following absorption, sodium iodide I 131 is distributed within the extra-cellular space. It is actively transported by the sodium-iodide symporter (NIS) protein and binds to thyroglobulin resulting in accumulation in the thyroid. The thyroid uptake of iodide is usually increased in hyperthyroidism and in goiter, and is decreased in hypothyroidism. Sodium iodide I 131 also accumulates in the stomach, choroid plexus, salivary glands breast, liver, gall bladder, and kidneys.

Elimination
Metabolism
In thyroid follicular cells, iodide is oxidized through the action of thyroid peroxidase to iodinium (I^+) which in turn iodinates tyrosine residues of thyroglobulin.

Excretion
Sodium iodide I 131 is excreted in urine and feces. The normal range of urinary excretion is 37% to 75% of the administered dose, varying with the thyroid and renal function of the patient. Fecal excretion is about 10%.

16 HOW SUPPLIED/STORAGE AND HANDLING

16.1 How Supplied

Each capsule contains 3.70 megabecquerels (100 microCi) at time of calibration. Half of each capsule is white, while the other half is either pink, yellow, orange, grey or green according to the manufactured lot.

- The capsules are packaged in plastic vials containing 5 capsules of the same strength and same color. (NDC 65174-461-05).
- Consult the color-coded decay calendar that is updated in January of each year to help you establish which colored capsules correspond to your prescribed dose: https://www.draximage.com/products/us/draximage-i-131-diagnostic-capsules/ or calculate the correct dosage from the date and time of calibration provided on the container label.
- The calibration date and expiration date are indicated on the vial container label.

16.2 Storage and Handling

Store Sodium Iodide I 131 Capsules Diagnostic between 15 °C and 30 °C (59 °F and 86 °F).

Store and dispose of Sodium Iodide I 131 Capsules Diagnostic in compliance with the appropriate regulations of the government agency authorized to license the use of this radionuclide.

This radiopharmaceutical is approved for use by persons under license by the Nuclear Regulatory Commission or the relevant regulatory authority of an Agreement State.

17 PATIENT COUNSELING INFORMATION

Administration Instructions

- Advise patients to hydrate before and after administration of Sodium Iodide I 131 Capsules Diagnostic and void frequently to ensure rapid excretion [see Dosage and Administration (2.2)].
- Advise patients to fast at least 2 hours before and 2 hours after administration to ensure absorption [see Dosage and Administration (2.2)].
- Advise patients to maintain a low-iodine diet two weeks prior to radioiodine administration and continue for several days during the uptake or imaging process [See Dosage and Administration (2.2) and Drug Interactions (7)].

Fetal Toxicity
Advise female patients of reproductive potential of the risk of neonatal hypothyroidism with fetal exposure [see Contraindications (4), Warnings and Precautions (5.1) and Use in Specific Populations (8.1, 8.3)].

Lactation
Advise women to discontinue breastfeeding after Sodium Iodide I 131 Capsules Diagnostic administration [see Use in Specific Populations (8.2)].

Manufactured by:
Jubilant DraxImage Inc., Kirkland, Québec, Canada, H9H 4J4.

Art Rev.: 2.1
Revised: February 2020